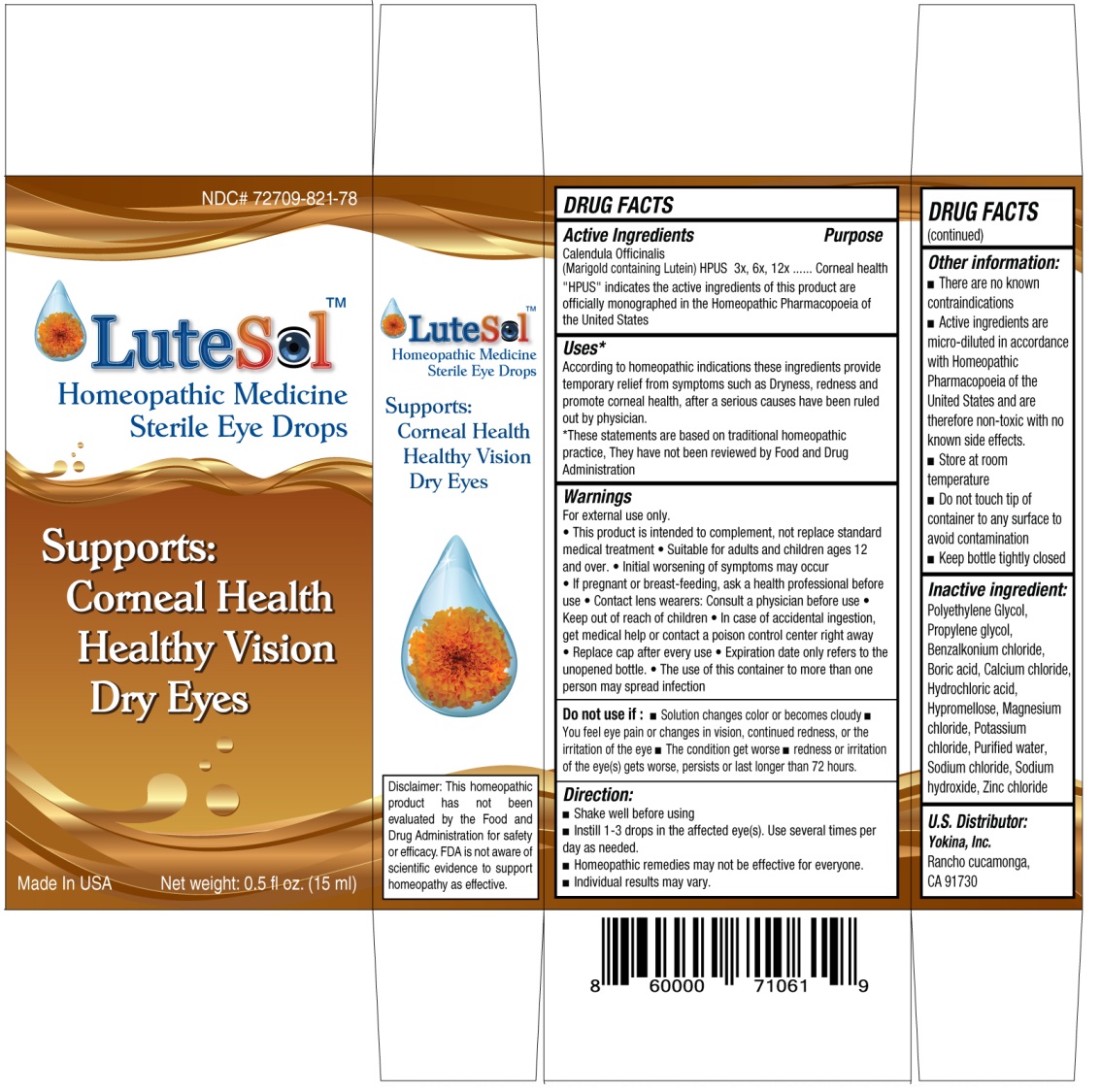 DRUG LABEL: LuteSol Homeopathic Medicine Sterile Eye Drops
NDC: 72709-821 | Form: SOLUTION/ DROPS
Manufacturer:  Yokina Inc. 
Category: homeopathic | Type: HUMAN OTC DRUG LABEL
Date: 20181220

ACTIVE INGREDIENTS: CALENDULA OFFICINALIS FLOWERING TOP 3 [hp_X]/15 mL
INACTIVE INGREDIENTS: POLYETHYLENE GLYCOL 400; PROPYLENE GLYCOL; BENZALKONIUM CHLORIDE; BORIC ACID; CALCIUM CHLORIDE; HYDROCHLORIC ACID; HYPROMELLOSE, UNSPECIFIED; MAGNESIUM CHLORIDE; POTASSIUM CHLORIDE; WATER; SODIUM CHLORIDE; SODIUM HYDROXIDE; ZINC CHLORIDE

LuteSol Homeopathic Medicine Sterile Eye Drops

Active Ingredients

Calendula Officinalis (Marigold containing Lutein), HPUS 3x, 6x, 12x

"HPUS" indicates the active ingredients of this product are officially monographed in the Homeopathic Pharmacopoeia of the United States

Purpose

Corneal health

Uses*

According to homeopathic indications these ingredients provide temporary relief from symptoms such as Dryness, redness and promote corneal health, after a serious causes have been ruled out by physician.

*These statements are based on traditional homeopathic practice. They have not been reviewed by Food and Drug Administration

Warnings

For external use only.

• This product is intended to complement, not replace standard medical treatment • Suitable for adults and children ages 12 and over. • Initial worsening of symptoms may occur • If pregnant or breast-feeding, ask a health professional before use • Contact lens wearers: Consult a physician before use • Replace cap after every use • Expiration date only refers to the unopened bottle. • The use of this container to more than one person may spread infection

Do not use if : • Solution changes color or becomes cloudy • You feel eye pain or changes in vision, continued redness, or the irritation of the eye • The condition get worse • redness or irritation of the eye(s) get worse, persists or last longer than 72 hours.

• Keep out of reach of children • In case of accidental ingestion, get medical help or contact a poison control center right away

Direction:

• Shake well before using

• Instill 1-3 drops in the affected eye(s). Use several times per day as needed.

• Homeopathic remedies may not be effective for everyone.

• Individual results may vary.

Other information:

• There are known contraindications

• Active ingredients are micro-diluted in accordance with Homeopathic Pharmacopoeia of the United States and are therefore non-toxic with no known side effects.

• Store at room temperature

• Do not touch tip of container to any surface to avoid contamination

• Keep bottle tightly closed

Inactive ingredient:

Polyethylene Glycol, Propylene glycol, Benzalkonium chloride, Boric acid, Calcium chloride, Hydrochloric acid, Hypromellose, Magnesium chloride, Potassium chloride, Purified water, Sodium chloride, Sodium hydroxide, Zinc chloride

Supports:

Corneal Health

Healthy Vision

Dry Eyes

Made In USA

U.S. Distributor:

Yokina Inc.

Rancho cucamonga,

CA 91730